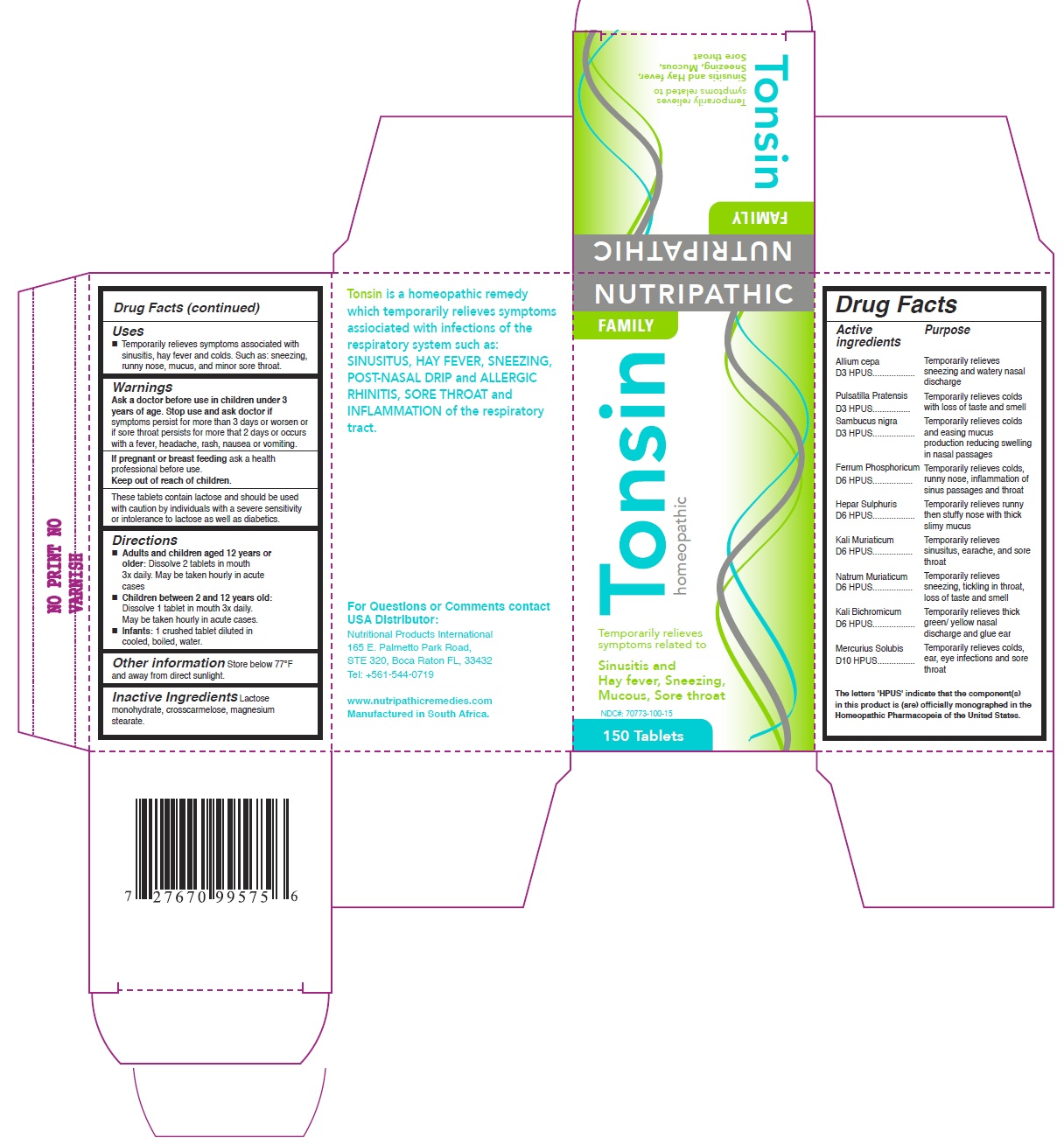 DRUG LABEL: Tonsin
NDC: 70773-100 | Form: TABLET
Manufacturer: PRIVATE LABEL BRANDS CC
Category: homeopathic | Type: HUMAN OTC DRUG LABEL
Date: 20171227

ACTIVE INGREDIENTS: SAMBUCUS NIGRA FLOWERING TOP 3 [hp_X]/100 [hp_X]; FERRUM PHOSPHORICUM 6 [hp_X]/100 [hp_X]; SODIUM CHLORIDE 6 [hp_X]/100 [hp_X]; POTASSIUM DICHROMATE 6 [hp_X]/100 [hp_X]; ALLIUM CEPA WHOLE 3 [hp_X]/100 [hp_X]; PULSATILLA PRATENSIS 3 [hp_X]/100 [hp_X]; CALCIUM SULFIDE 6 [hp_X]/100 [hp_X]; POTASSIUM CHLORIDE 6 [hp_X]/100 [hp_X]; MERCURIUS SOLUBILIS 10 [hp_X]/100 [hp_X]
INACTIVE INGREDIENTS: LACTOSE MONOHYDRATE; CROSCARMELLOSE; MAGNESIUM STEARATE

ACTIVE INGREDIENTS (OTC- ACTIVE INGREDIENT SECTION)

Allium cepa D3 HPUS

Pulsatilla Pratensis D3 HPUS

Sambucus nigra D3 HPUS

Ferrum Phosphoricum D6 HPUS

Hepar Sulphuris D6 HPUS

Kali Muriaticum D6 HPUS

Natrum Muriaticum D6 HPUS

Kali Bichromicum D6 HPUS

Mercurius Solubis D10 HPUS

PURPOSE (DOSAGE & ADMINISTRATION SECTION)

Temporarily relieves sneezing and watery nasal discharge

Temporarily relieves colds with loss of taste and smell

Temporarily relieves colds and easing mucus production reducing swelling in nasal passages

Temporarily relieves colds, runny nose, inflammation of sinus passages and throat

Temporarily relieves runny then stuffy nose with thick slimy mucus

Temporarily relieves sinusitus, earache, and sore throat

Temporarily relieves sneezing, tickling in throat loss of taste and smell

Temporarily relieves thick green/ yellow nasal discharge and glue ear

Temporarily relieves colds, ear, eye infections and sore throat

USES (OTC- PURPOSE SECTION)

Temporarily relieves symptoms associated with sinusitis, hay fever and colds. Such as: sneezing, runny nose, mucus, and minor sore throat.

KEEP OUT OF REACH OF CHILDREN (OTC- KEEP OUT OF REACH OF CHILDREN SECTION)

KEEP OUT OF REACH OF CHILDREN

DIRECTIONS (INDICATIONS & USAGE SECTION)

Adults and children aged 12 years or older:

Dissolve 2 tablets in mouth 3x daily. May be taken hourly in acute cases

Children between 2 and 12 years old:

Dissolve 1 tablet in mouth 3x daily. May be taken hourly in acute cases.

Infants: 1 crushed tablet diluted in cooled, boiled, water.

OTHER INFORMATION (INSTRUCTIONS FOR USE SECTION)

Store below 77°F and away from direct sunlight.

WARNING (WARNINGS SECTION)

These tablets contain lactose and should be used with caution by individuals with a severe sensitivity or intolerance to lactose as well as diabetics.

STOP USE AND ASK DOCTOR IF (OTC- STOP USE SECTION)

if symptoms persist for more than 3 days or worsen or if sore throat persists for more that 2 days or occurs with a fever, headache, rash, nausea or vomiting.

ASK A DOCTOR (OTC- ASK DOCTOR SECTION)

ASK A DOCTOR BEFORE USING IN CHILDREN UNDER 3 YEARS OF AGE

IF PREGNANT OR BREASTFEEDING, (OTC- PREGNANCY OR BREAST FEEDING SECTION)

ask a health professional before use.

INACTIVE INGREDIENTS (INACTIVE INGREDIENT SECTION)

Lactose monohydrate, crosscarmelose, magnesium stearate.